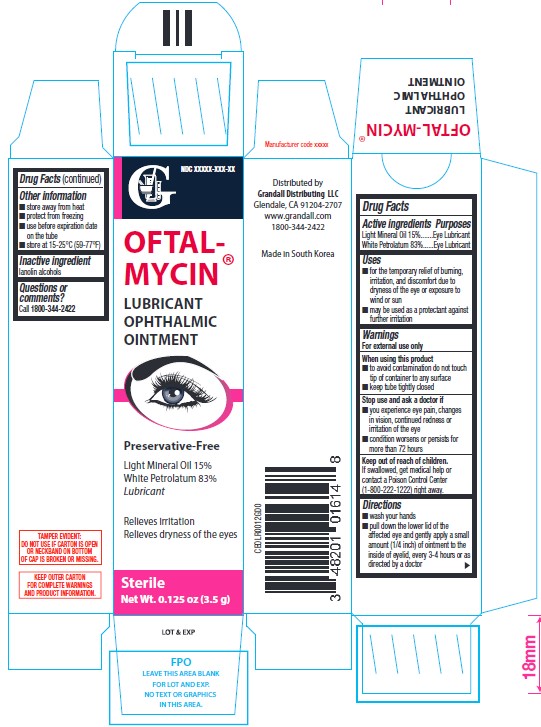 DRUG LABEL: OFTAL-MYCIN LUBRICANT OPHTHALMIC
NDC: 48201-301 | Form: OINTMENT
Manufacturer: GRANDALL DISTRIBUTING, LLC
Category: otc | Type: HUMAN OTC DRUG LABEL
Date: 20251027

ACTIVE INGREDIENTS: WHITE PETROLATUM 83 g/100 g; LIGHT MINERAL OIL 15 g/100 g
INACTIVE INGREDIENTS: LANOLIN ALCOHOLS

Grandall (as PLD) - Oftal-Mycin Lubricant Ophthalmic Ointment (48201-301)

ACTIVE INGREDIENT

Light Mineral Oil 15%

White Petrolatum 83%

PURPOSE

EYE LUBRICANT

USES

- for the temporary relief of burning, irritation, and discomfort due to dryness of the eye or exposure to wind or sun
- may be used as a protectant against further irritation

WARNINGS

For external use only

When using this product

- to avoid contamination do not touch tip of container to any surface
- keep tube tightly closed

Stop use and ask a doctor if

- you experience eye pain, changes in vision, continued redness or irritation of the eye
- condition worsens or persists for more than 72 hours

Keep out of reach of children. If swallowed, get medical help or contact a Poison Control Center (1-800-222-1222) right away.

DIRECTIONS

- wash your hands
- pull down the lower lid of the affected eye and gently apply a small amount (1/4 inch) of ointment to the inside of eyelid, every 3-4 hours or as directed by a doctor

OTHER INFORMATION

- store away from heat
- protect from freezing
- use before expiration date on the tube
- store at 15-25°C (59-77°F)

INACTIVE INGREDIENT

LANOLIN ALCOHOLS

QUESTIONS OR COMMENTS?

CALL 1800-344-2422